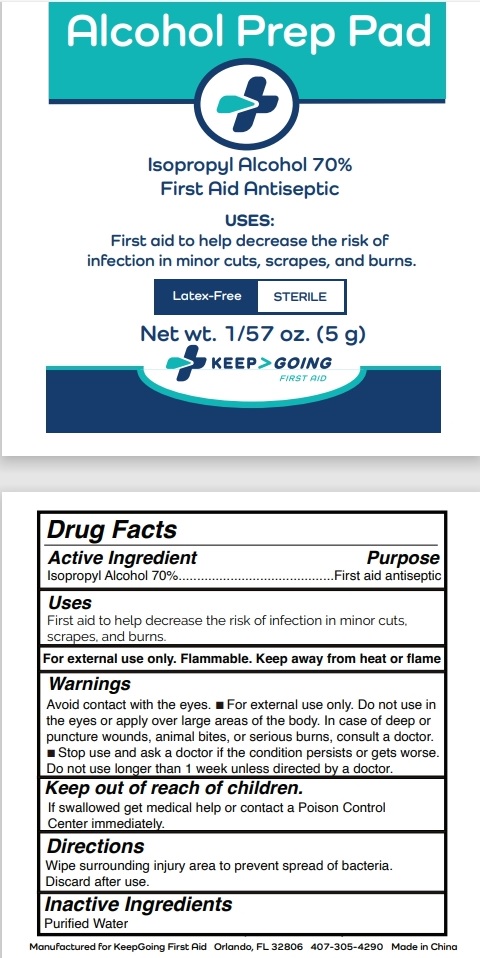 DRUG LABEL: Keep Going Alcohol Prep Pad
NDC: 71734-341 | Form: CLOTH
Manufacturer: JIANGMEN SHUIZIRUN SANITARY ARTICLES CO., LTD.
Category: otc | Type: HUMAN OTC DRUG LABEL
Date: 20240808

ACTIVE INGREDIENTS: ISOPROPYL ALCOHOL 70 g/100 g
INACTIVE INGREDIENTS: WATER

DRUG FACTS

Active Ingredient

Isopropyl Alcohol ................ 70%

Purpose

Antiseptic Cleanser

Uses:

Disinfects and eliminates germs.

Warnings

DO NOT USE

Flammable. Keep away from fire or flame.

For external use only.

- Do not use in the eyes. If irritation or redness occurs, stop use.
- Direct contact with open wound will cause stinging.

Keep out of reach of children.

If swallowed get medical help or contact a Posion Control Center immediately.

Directions

Wipe surrounding injury area to prevent spread of bacteria. Discard after use.

Inactive Ingredients:

Purified Water